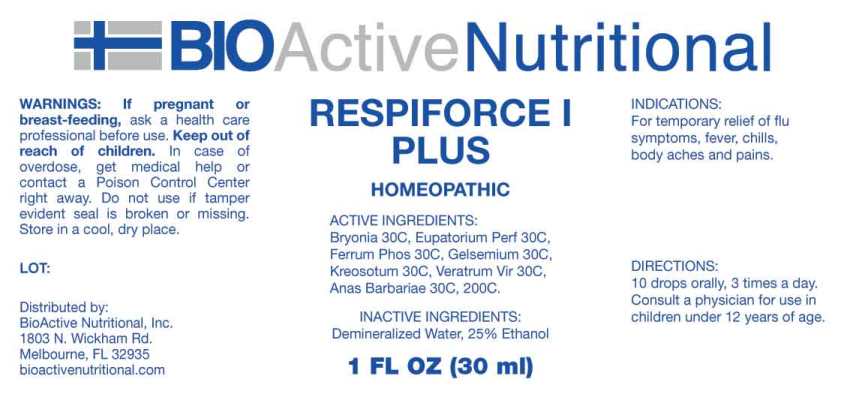 DRUG LABEL: Respiforce I Plus
NDC: 43857-0598 | Form: LIQUID
Manufacturer: BioActive Nutritional, Inc.
Category: homeopathic | Type: HUMAN OTC DRUG LABEL
Date: 20241018

ACTIVE INGREDIENTS: BRYONIA ALBA ROOT 30 [hp_C]/1 mL; EUPATORIUM PERFOLIATUM FLOWERING TOP 30 [hp_C]/1 mL; FERROSOFERRIC PHOSPHATE 30 [hp_C]/1 mL; GELSEMIUM SEMPERVIRENS ROOT 30 [hp_C]/1 mL; WOOD CREOSOTE 30 [hp_C]/1 mL; VERATRUM VIRIDE ROOT 30 [hp_C]/1 mL; CAIRINA MOSCHATA HEART/LIVER AUTOLYSATE 30 [hp_C]/1 mL
INACTIVE INGREDIENTS: WATER; ALCOHOL

DRUG FACTS:

ACTIVE INGREDIENTS:

Bryonia (Alba) 30C, Eupatorium Perfoliatum 30C, Ferrum Phosphoricum 30C, Gelsemium Sempervirens 30C, Kreosotum 30C, Veratrum Viride 30C, Anas Barbariae, Hepatis ET Cordis Extractum 30C, 200C.

INDICATIONS:

For temporary relief of flu symptoms, fever, chills, body aches and pains.

WARNINGS:

If pregnant or breast-feeding, ask a health care professional before use.

Keep out of reach of children. In case of overdose, get medical help or contact a Poison Control Center right away.

Do not use if tamper evident seal is broken or missing.

Store in cool, dry place.

Keep out of reach of children. In case of overdose, get medical help or contact a Poison Control Center right away.

DIRECTIONS:

10 drops orally, 3 times a day. Consult a physician for use in children under 12 years of age.

INDICATIONS:

For temporary relief of flu symptoms, fever, chills, body aches and pains.

INACTIVE INGREDIENTS:

Demineralized Water, 25% Ethanol

QUESTIONS:

Distributed by:
BioActive Nutritional, Inc.
1803 N. Wickham Rd.
Melbourne, FL 32935
bioactivenutritional.com

PACKAGE LABEL DISPLAY:

BIOActive Nutritional

RESPIFORCE I PLUS

HOMEOPATHIC

1 FL OZ (30 ml)